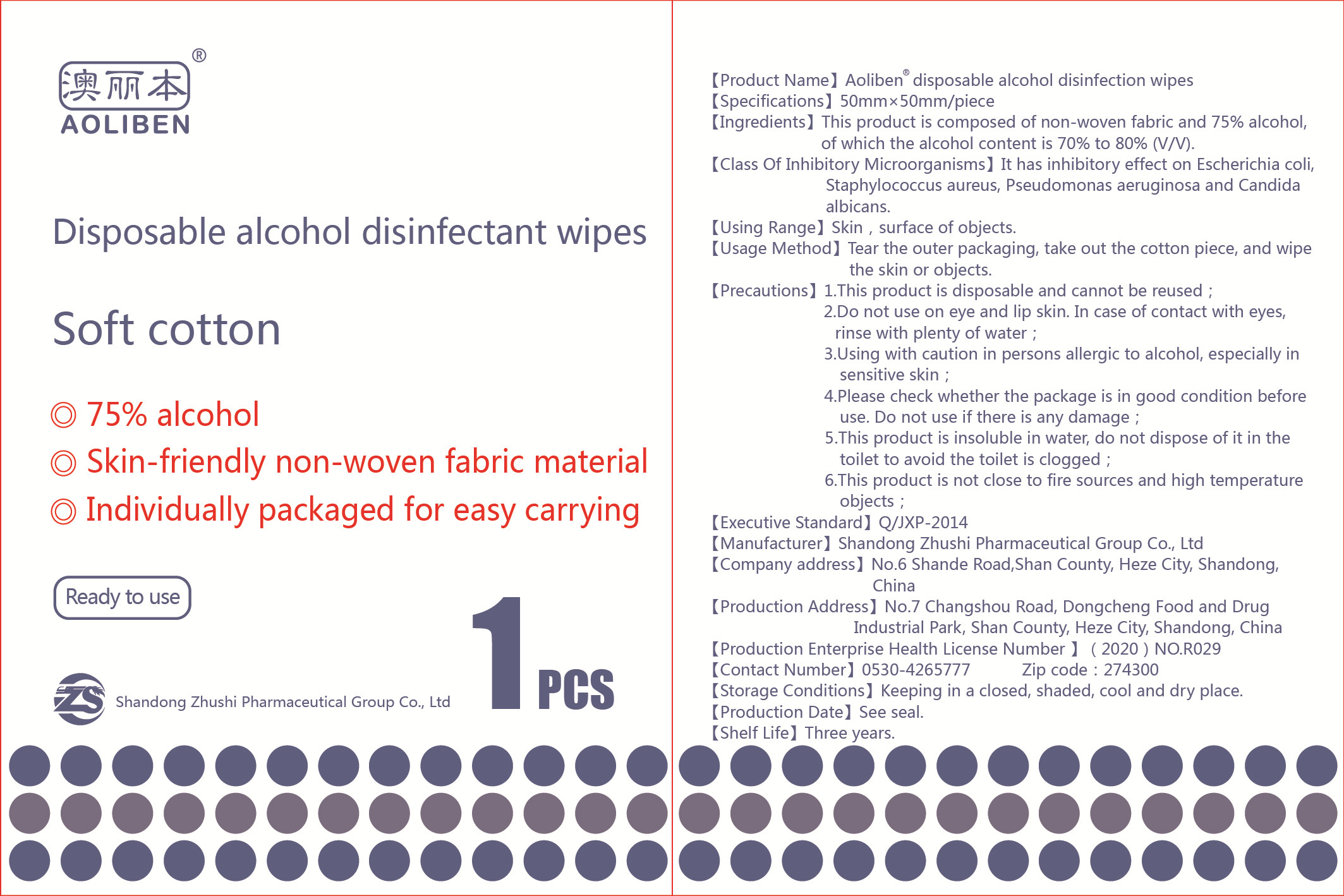 DRUG LABEL: Aoliben disposable alcohol disinfectant wipes
NDC: 56040-009 | Form: CLOTH
Manufacturer: Shandong Zhushi Pharmaceutical Group Co., Ltd.
Category: otc | Type: HUMAN OTC DRUG LABEL
Date: 20220228

ACTIVE INGREDIENTS: ALCOHOL 3 mL/1 1
INACTIVE INGREDIENTS: WATER

DOSAGE AND ADMINISTRATION

Keeping in a closed, shaded, cool and dry place.

INACTIVE INGREDIENT

Purified water,Non-woven fabric

INDICATIONS AND USAGE

Tear the outer packaging, take out the cotton piece, and wipe the skin or objects.

ACTIVE INGREDIENT

Alcohol

keep out of reach of children

PURPOSE

Disinfection
Sterilization
No Rinseing

WARNINGS

1.This product is disposable and cannot be reused ;
2.Do not use on eye and lip skin. In case of contact with eyes,rinse with plenty of water ;
3.Using with caution in persons allergic to alcohol, especially in sensitive skin ;
4.Please check whether the package is in good condition before use. Do not use if there is any damage ;
5.This product is insoluble in water, do not dispose of it in the toilet to avoid the toilet is clogged ;
6.This product is not close to fire sources and high temperature objects ;